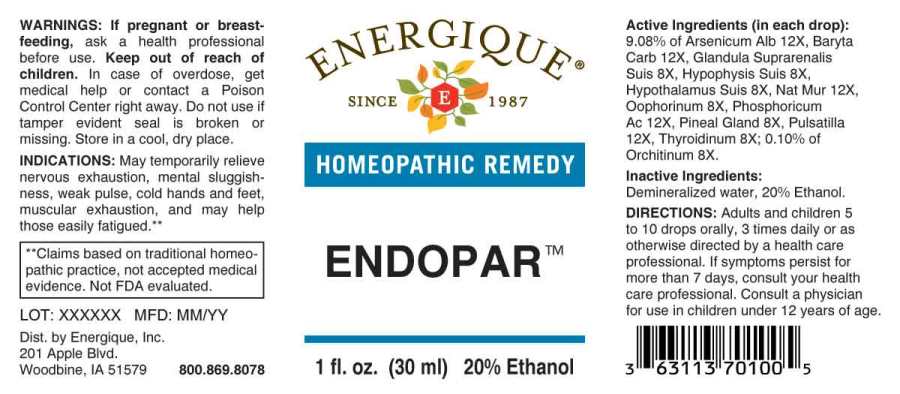 DRUG LABEL: Endopar
NDC: 44911-0440 | Form: LIQUID
Manufacturer: Energique, Inc.
Category: homeopathic | Type: HUMAN OTC DRUG LABEL
Date: 20231121

ACTIVE INGREDIENTS: SUS SCROFA ADRENAL GLAND 8 [hp_X]/1 mL; SUS SCROFA PITUITARY GLAND 8 [hp_X]/1 mL; SUS SCROFA HYPOTHALAMUS 8 [hp_X]/1 mL; SUS SCROFA OVARY 8 [hp_X]/1 mL; BOS TAURUS TESTICLE 8 [hp_X]/1 mL; SUS SCROFA PINEAL GLAND 8 [hp_X]/1 mL; THYROID 8 [hp_X]/1 mL; ARSENIC TRIOXIDE 12 [hp_X]/1 mL; BARIUM CARBONATE 12 [hp_X]/1 mL; SODIUM CHLORIDE 12 [hp_X]/1 mL; PHOSPHORIC ACID 12 [hp_X]/1 mL; PULSATILLA PRATENSIS WHOLE 12 [hp_X]/1 mL
INACTIVE INGREDIENTS: WATER; ALCOHOL

DRUG FACTS:

ACTIVE INGREDIENTS:

(in each drop): 9.08% Arsenicum Album 12X, Baryta Carbonica 12X, Glandula Suprarenalis Suis 8X, Hypophysis Suis 8X, Hypothalamus Suis 8X, Natrum Muriaticum 12X, Oophorinum (Suis) 8X, Phosphoricum Acidum 12X, Pineal Gland 8X, Pulsatilla (Pratensis) 12X, Thyroidinum 8X; 0.10% of Orchitinum (Bovine) 8X.

INDICATIONS:

May temporarily relieve nervous exhaustion, mental sluggishness, weak pulse, cold hands and feet, muscular exhaustion, and may help those easily fatigued.**
**Claims based on traditional homeopathic practice, not accepted medical evidence. Not FDA evaluated.

WARNINGS:

If pregnant or breast-feeding, ask a health professional before use.
Keep out of reach of children. In case of overdose, get medical help or contact a Poison Control Center right away.
Do not use if tamper evident seal is broken or missing. Store in a cool, dry place.

KEEP OUT OF REACH OF CHILDREN:

In case of overdose, get medical help or contact a Poison Control Center right away.

DIRECTIONS:

Adults and children 5 to 10 drops orally, 3 times daily or as otherwise directed by a health care professional. If symptoms persist for more than 7 days, consult your health care professional. Consult a physician for use in children under 12 years of age.

INDICATIONS:

May temporarily relieve nervous exhaustion, mental sluggishness, weak pulse, cold hands and feet, muscular exhaustion, and may help those easily fatigued.**
**Claims based on traditional homeopathic practice, not accepted medical evidence. Not FDA evaluated.

INACTIVE INGREDIENTS:

Demineralized water, 20% Ethanol.

QUESTIONS:

Dist. by Energique, Inc.
201 Apple Blvd
Woodbine, IA 51579 800.869.8078

PACKAGE LABEL DISPLAY:

ENERGIQUE
SINCE 1987
HOMEOPATHIC REMEDY
ENDOPAR
1 fl. oz. (30 ml)